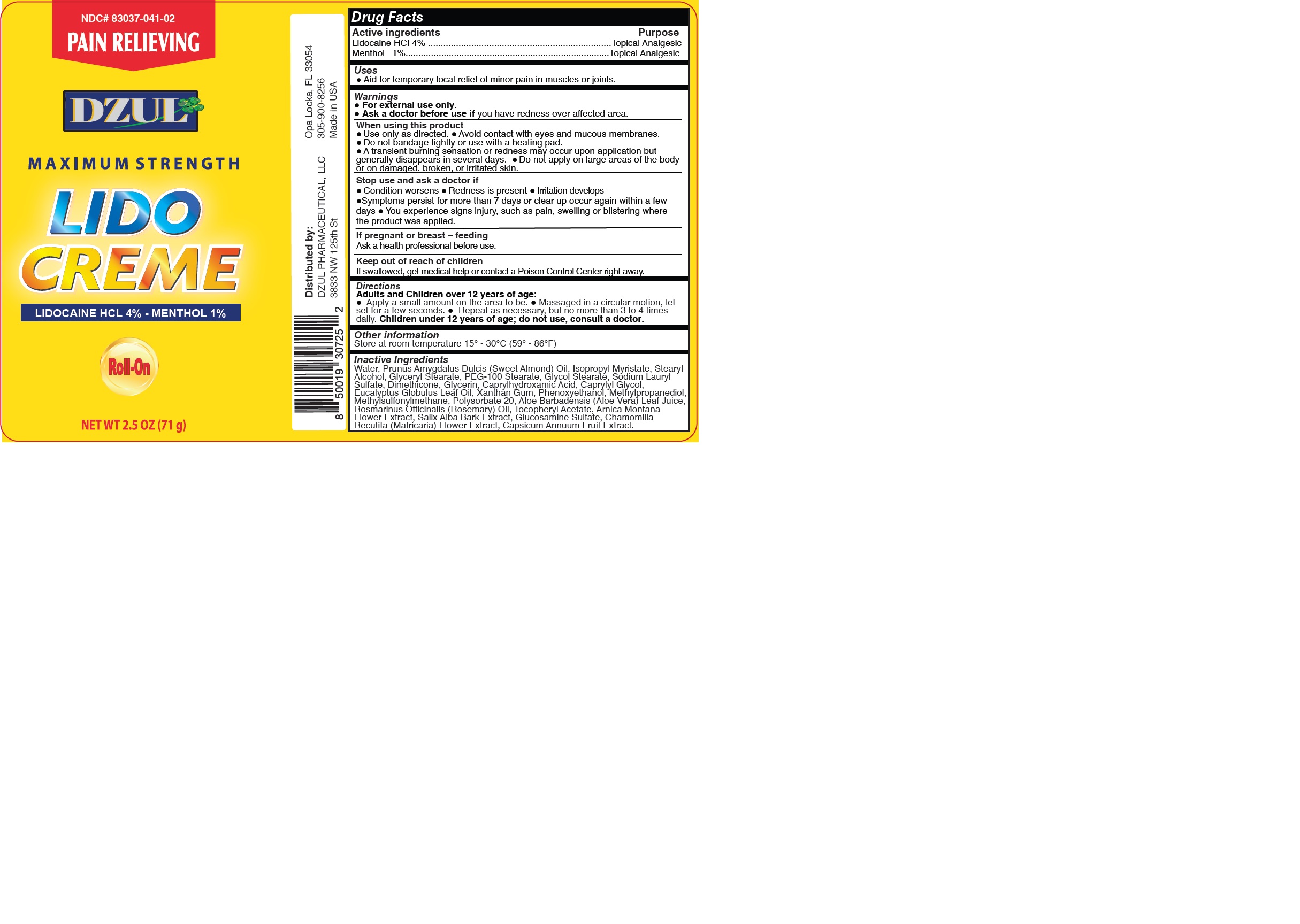 DRUG LABEL: DZUL - LIDO CREME
NDC: 83037-041 | Form: LOTION
Manufacturer: Caball Sales, Inc.
Category: otc | Type: HUMAN OTC DRUG LABEL
Date: 20230925

ACTIVE INGREDIENTS: MENTHOL 1 g/100 g; LIDOCAINE HYDROCHLORIDE 4 g/100 g
INACTIVE INGREDIENTS: ALMOND OIL; DIMETHYL SULFONE; ISOPROPYL MYRISTATE; METHYLPROPANEDIOL; ARNICA MONTANA FLOWER; .ALPHA.-TOCOPHEROL ACETATE; WATER; PEG-100 STEARATE; STEARYL ALCOHOL; GLYCOL STEARATE; SODIUM LAURYL SULFATE; GLYCERIN; DIMETHICONE 1000; CAPRYLHYDROXAMIC ACID; CAPRYLYL GLYCOL; PHENOXYETHANOL; ALOE VERA LEAF; GLYCERYL STEARATE SE; EUCALYPTUS GLOBULUS LEAF; ROSEMARY OIL; CHAMOMILE; SALIX ALBA BARK; CAPSICUM ANNUUM WHOLE; XANTHAN GUM; POLYSORBATE 20; GLUCOSAMINE SULFATE

83037-041-02

ACTIVE INGREDIENT

Lidocaine HCl 4%

Menthol 1%

PURPOSE

Topical Analgesic

USES:

For temporary local relief of minor pain in muscles or joints.

WARNINGS

For external use only.

Ask a doctor before use if you have redness over affected area.

WHEN USING

Use only as directed.
Avoid contact with eyes and mucous membranes.
Do not bandage tightly or use with a heating pad.
A transient burning sensation or redness may occur upon application but generally disappears in several days.

Do not apply on large areas of the body or on damaged, broken, or irritated skin.

STOP USE AND ASK A DOCTOR IF:

Redness is present.
Condition worsens.
Irritation develops.
Symptoms persist for more than 7 days or clear up and occur again within a few days.

You experience signs injury, such as pain, swelling or blistering where the product was applied.

PREGNANCY OR BREAST FEEDING

Ask a health professional before use.

KEEP OUT OF REACH OF CHILDREN

If swallowed, get medical help or contact a Poison Control Center right away.

DIRECTIONS:

Adults and children over 12 years of age

Apply a small amount to the affected area.
Massage in a circular motion, let set for a few seconds.
Repeat as necessary, but no more than 3 to 4 times daily.

Children under 12 years of age; do not use unless directed by doctor.

OTHER SAFETY INFORMATION

Store at room temperature 15° - 30°C (59° - 86°F)

INACTIVE INGREDIENT

Water, Prunus Amygdalus Dulcis (Sweet Almond) Oil, Isopropyl Myristate, Glycol Stearate, Stearyl Alcohol, Glyceryl Stearate, PEG-100 Stearate, Sodium Lauryl Sulfate, Dimethicone, Glycerin, Caprylhydroxamic Acid, Caprylyl Glycol, Eucalyptus Globulus Leaf Oil, Phenoxyethanol, Methylpropanediol, Acrylamide/Sodium Acrylate Copolymer, Paraffinum Liquidum, Trideceth-6, Methylsulfonylmethane, Aloe Barbadensis (Aloe Vera) Leaf Juice, Rosmarinus Officinalis (Rosemary) Oil, Tocopheryl Acetate, Arnica Montana Flower Extract, Salix Alba Bark Extract, Glucosamine Sulfate, Chamomilla Recutita (Matricaria) Flower Extract, Capsicum Annuum Fruit Extract.